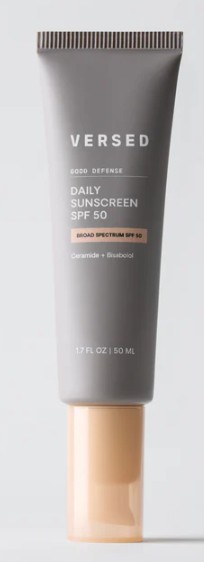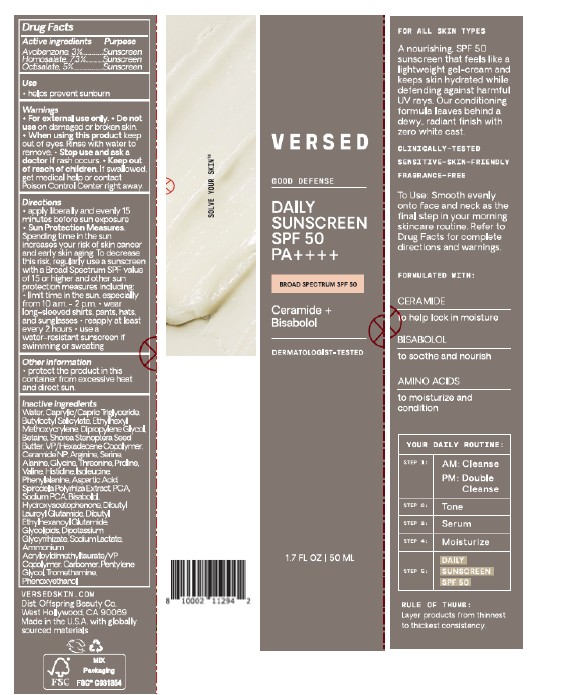 DRUG LABEL: VERSED DAILY SUNSCREEN SPF 50
NDC: 68577-203 | Form: CREAM
Manufacturer: COSMAX USA, CORP
Category: otc | Type: HUMAN OTC DRUG LABEL
Date: 20251222

ACTIVE INGREDIENTS: AVOBENZONE 3 mg/100 mL; HOMOSALATE 7.3 mg/100 mL; OCTISALATE 5 mg/100 mL
INACTIVE INGREDIENTS: THREONINE; PHENYLALANINE; SHOREA STENOPTERA SEED BUTTER; SODIUM PCA; TROMETHAMINE; PENTYLENE GLYCOL; VP/HEXADECENE COPOLYMER; GLYCINE; VALINE; HISTIDINE; ALANINE; SERINE; BISABOLOL; DIBUTYL ETHYLHEXANOYL GLUTAMIDE; DIBUTYL LAUROYL GLUTAMIDE; CARBOMER; DIPOTASSIUM GLYCYRRHIZATE; SODIUM LACTATE; ARGININE; PHENOXYETHANOL; BUTYLOCTYL SALICYLATE; AMMONIUM ACRYLOYLDIMETHYLTAURATE/VP COPOLYMER; SPIRODELA POLYRHIZA; ISOLEUCINE; PROLINE; WATER; HYDROXYACETOPHENONE; CAPRYLIC/CAPRIC TRIGLYCERIDE; BETAINE; CERAMIDE NP; ASPARTIC ACID; DIPROPYLENE GLYCOL; ETHYLHEXYL METHOXYCRYLENE; PCA

VERSED DAILY SUNSCREEN SPF 50

Active ingredients

Avobenzone 3%

Homosalate 7.3%

Octisalate 5%

Purpose

Sunscreen

USES

Use

- helps prevent sunburn

Warnings

- For external use only

Do not use on damaged or broken skin

- When using this product keep out of eyes. Rinse with water to remove.

Stop use and ask a doctor if rash occurs.

Keep out of reach of children. If product is swallowed, get medical help or contact a Poison Control center right away.

DIRECTIONS

- Apply generously and evenly 15 minutes before sun exposure.
- Sun Protection Measures. Spending time in the sun increases your risk of skin cancer and early skin aging. To decrease this risk, regularly use a sunscreen with a Broad Spectrum SPF value of 15 or higher and other sun protection measures including:
- Limit time in the sun, especially from 10am-2pm
- Wear long-sleeved shirts, pants, hats, and sunglasses.
- Reapply at least every 2 hours
- Use a water resistant sunscreen if swimming or sweating.

OTHER INFORMATION

- Protect the product in this container from excessive heat and direct sun

Inactive Ingredients

Water, Caprylic/Capric Triglyceride, Butyloctyl Salicylate, Ethylhexyl Methoxycrylene, Dipropylene Glycol, Betaine, Shorea Stenoptera Seed Butter, VP/Hexadecene Copolymer, Ceramide NP, Arginine, Serine, Alanine, Glycine, Threonine, Proline, Valine, Histidine, Isoleucine, Phenylalanine, Aspartic Acid, Spirodela Polyrhiza Extract, PCA, Sodium PCA, Bisabolol, Hydroxyacetophenone, Dibutyl Lauroyl Glutamide, Dibutyl Ethylhexanoyl Glutamide, Glycolipids, Dipotassium Glycyrrhizate, Sodium Lactate, Ammonium Acryloyldimethyltaurate/VP Copolymer, Carbomer, Pentylene Glycol, Tromethamine, Phenoxyethanol